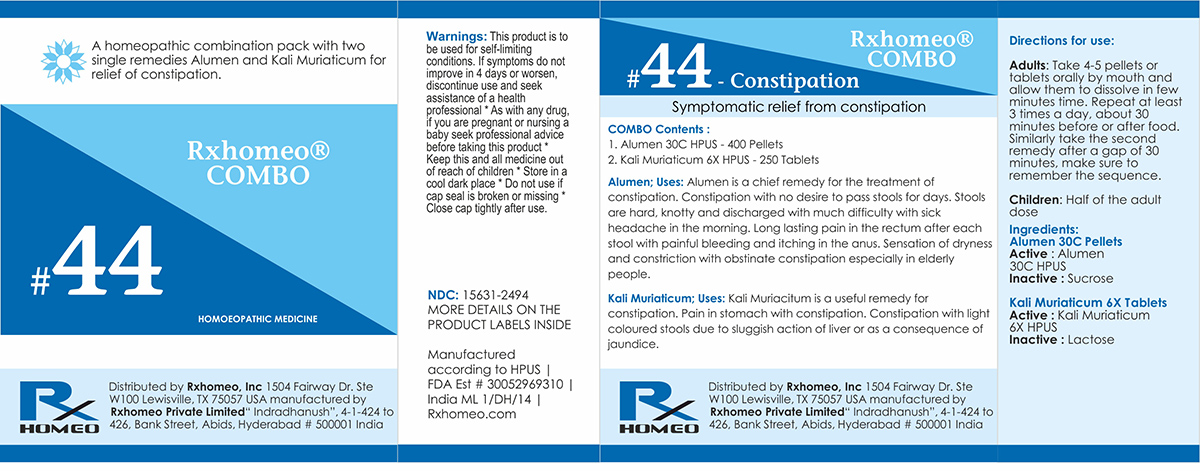 DRUG LABEL: Rxhomeo Homeopathic Combo
NDC: 15631-2494 | Form: KIT | Route: ORAL
Manufacturer: Rxhomeo Private Limited d.b.a.
Category: homeopathic | Type: HUMAN OTC DRUG LABEL
Date: 20161016

ACTIVE INGREDIENTS: POTASSIUM ALUM 3 [hp_X]/1 1; POTASSIUM CHLORIDE 1 [hp_X]/1 1
INACTIVE INGREDIENTS: SUCROSE; SUCROSE

ACTIVE INGREDIENT

ALUMEN HPUS 3X and higher

KALI MURIATICUM HPUS 1X and higher

USES

A homeopathic combination pack with two single remedies Alumen and Kali Muriaticum for relief of constipation.

Alumen;Uses: Alumen is a chief remedy for the treatment of constipation. Constipation with no desire to pass stools for days. Stools are hard, knotty and discharged with much difficulty with sick headache in the morning. Long lasting pain in the rectum after each stool with painful bleeding and itching in the anus. Sensation of dryness and constriction with obstinate constipation especially in elderly people.

Kali Muriaticum;Uses: Kali Muriacitum is a useful remedy for constipation. Pain in stomach with constipation. Constipation with light coloured stools due to sluggish action of liver or as a consequence of jaundice.

INDICATIONS

Condition listed above or as directed by the physician

DOSAGE

PELLETS included in the Combo

Adults- Take 4 or 6 Pellets by mouth, three times daily or as suggested by physician. Children 2 years and older- take 1/2 the adult dose.

TABLETS included in the Combo
Adults- Take 4 or 6 Tablets by mouth, three times daily or as suggested by physician. Children 2 years and older- take 1/2 the adult dose.

WARNINGS

This product is to be used for self-limiting conditions

STOP USE

If symptoms do not improve in 4 days, or worsen, discontinue use and seek assistance of health professional

KEEP OUT OF REACH OF CHILDREN

Keep this and all medication out of reach of children

Do not use if capseal is broken or missing.

Close the cap tightly after use.

INACTIVE INGREDIENTS

Sucrose for Pellets.

Lactose for Tablets.

STORAGE

Store in a cool dark place

QUESTIONS OR COMMENTS

www.Rxhomeo.com | 1.888.2796642 | info@rxhomeo.com
Rxhomeo, Inc 1504 Fairway Dr. Ste W 100 Lewisville, TX 75057 USA